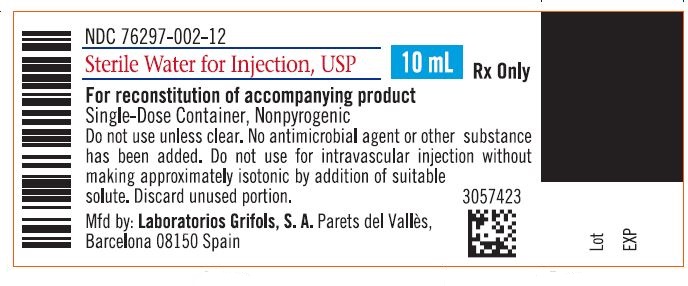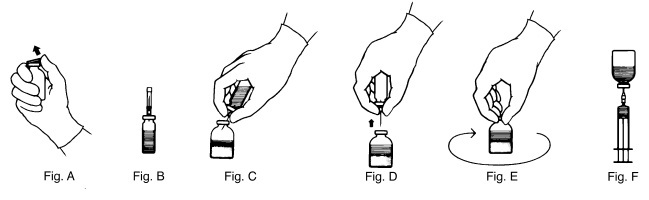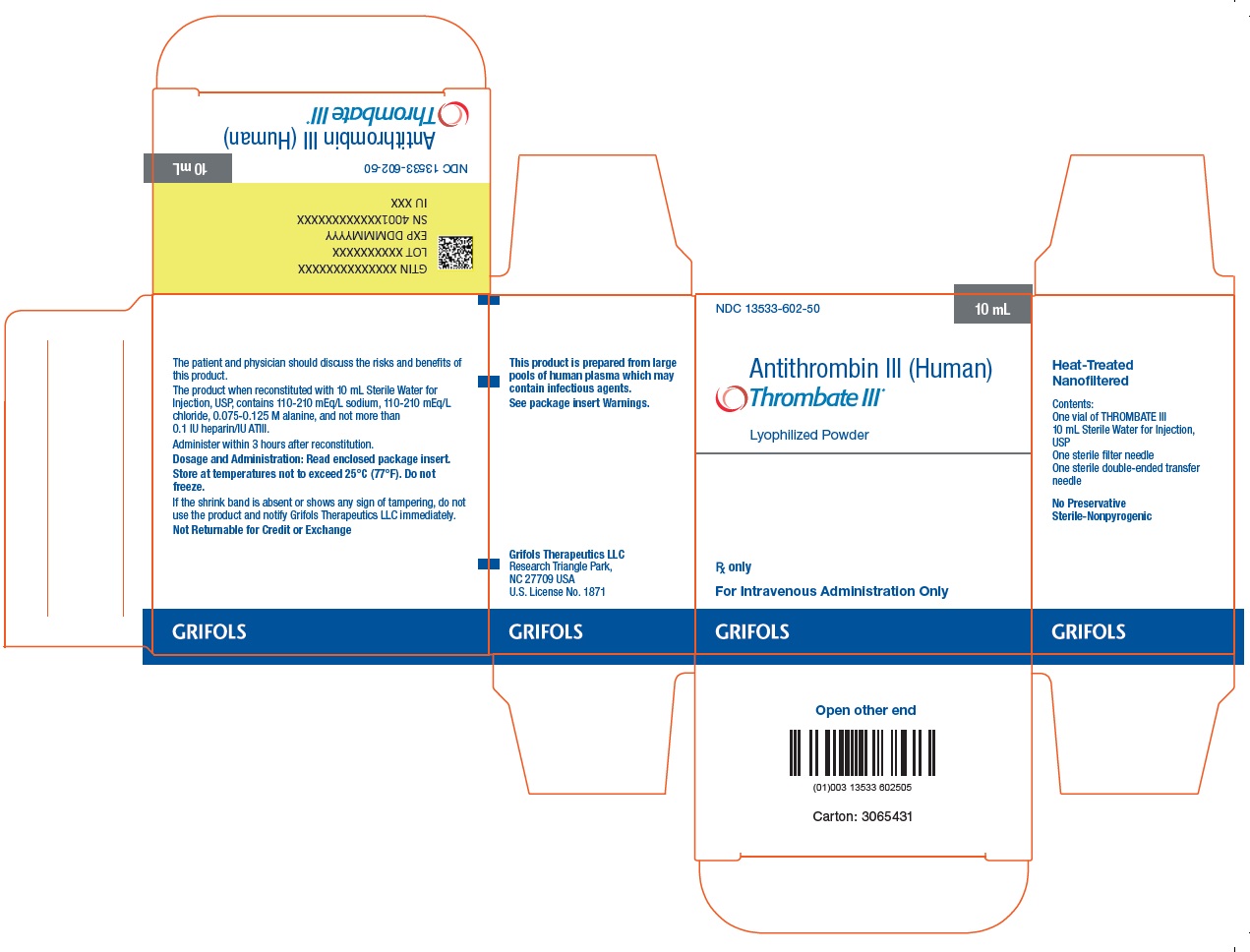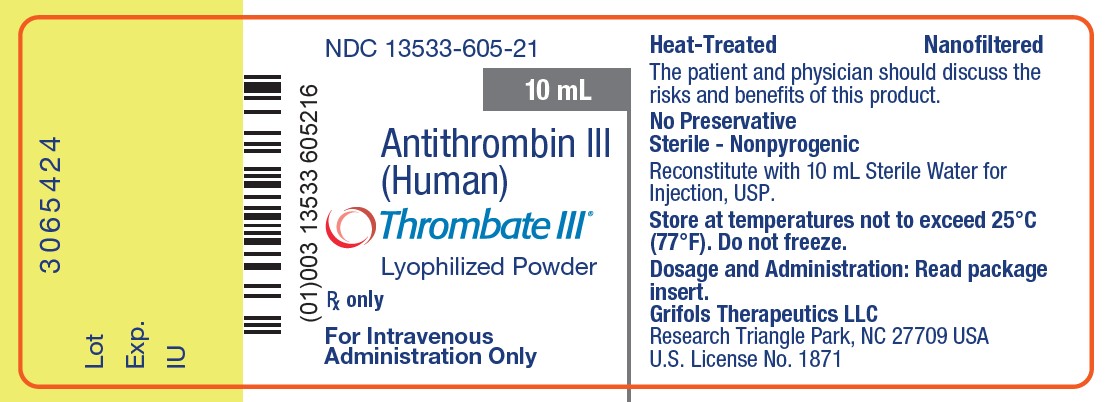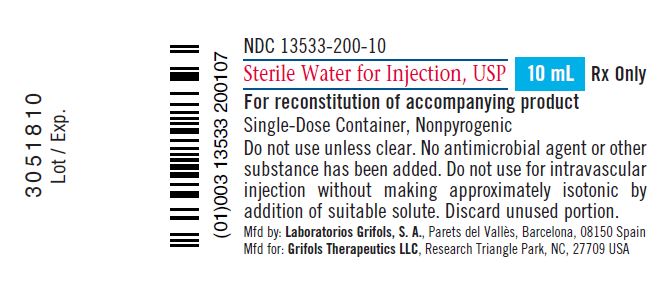 DRUG LABEL: THROMBATE III 
NDC: 13533-603 | Form: KIT | Route: INTRAVENOUS
Manufacturer: GRIFOLS USA, LLC
Category: other | Type: PLASMA DERIVATIVE
Date: 20250821

ACTIVE INGREDIENTS: Antithrombin Iii Human 50 [iU]/1 mL
INACTIVE INGREDIENTS: Alanine; Sodium Chloride; Water

HIGHLIGHTS OF PRESCRIBING INFORMATION

These highlights do not include all the information needed to use THROMBATE III safely and effectively. See full prescribing information for THROMBATE III.
THROMBATE III [antithrombin III (human)]
Lyophilized Powder for Solution for Intravenous Injection
Initial U.S. Approval: 1991

1 INDICATIONS AND USAGE

THROMBATE III is a human antithrombin (AT) indicated in adult and pediatric patients with hereditary antithrombin deficiency for:

- Treatment and prevention of thromboembolism
- Prevention of peri-operative and peri-partum thromboembolism (1)

RECENT MAJOR CHANGES

Indications and Usage (1) 7/2025

2 DOSAGE AND ADMINISTRATION

For intravenous use after reconstitution only

- Individualize dose to achieve AT level of 80% to 120% of normal human plasma. (2.1)

Dose | Target AT Level | Dose (Units) | Monitor AT Level
Loading | 120% of normal | 120 % - baseline % x body weight (kg) divided by 1.4% | - baseline - 20 minutes (peak) post-injection - 12 hours post-injection - pre-injection (trough)
Adjustment (as needed) | 80% to 120% of normal | Target % - trough % x body weight (kg) divided by 1.4% | - 20 minutes (peak) post-injection - at least every 12 hours post-injection - pre-injection (trough)
Maintenance (every 24 hours, as needed) | 80% to 120% of normal | Loading Dose x 0.6 | - approximately every 24 hours, as needed

Adapt the rate of administration to the response of the patient; typically the full dose is given over 10 to 20 minutes. (2.3)

3 DOSAGE FORMS AND STRENGTHS

For injection: approximately 500 units, lyophilized powder in single-dose vial for reconstitution. (3)

4 CONTRAINDICATIONS

None. (4)

5 WARNINGS AND PRECAUTIONS

- Hypersensitivity reactions, including anaphylaxis, are possible. Should symptoms occur, discontinue THROMBATE III infusion and begin appropriate treatment. (5.1)
- Because THROMBATE III is made from human blood, it may carry a risk of transmitting infectious agents, e.g., viruses, the variant Creutzfeldt-Jakob disease (vCJD) agent and, theoretically, the Creutzfeldt-Jakob disease (CJD) agent. (5.2)
- Perform coagulation tests to avoid excessive or insufficient anticoagulation and monitor for bleeding or thrombosis. Measure functional plasma AT levels with amidolytic or clotting assays; do not use immunoassays. (5.3)

6 ADVERSE REACTIONS

The most common adverse reactions (≥ 5% of patients) were dizziness, chest discomfort, nausea, dysgeusia, and pain (cramps). (6)

To report SUSPECTED ADVERSE REACTIONS, contact Grifols Therapeutics LLC at 1-800-520-2807 or FDA at 1-800-FDA-1088 or www.fda.gov/medwatch.

7 DRUG INTERACTIONS

The anticoagulant effect of heparin is enhanced by concurrent treatment with THROMBATE III. To avoid bleeding, reduce the dosage of heparin. (7)

8 USE IN SPECIFIC POPULATIONS

Pregnancy: suspend heparin administration and continue THROMBATE III administration during labor and delivery. (8.1)

FULL PRESCRIBING INFORMATION

1 INDICATIONS AND USAGE

THROMBATE III is indicated in adult and pediatric patients with hereditary antithrombin deficiency for:

- Treatment and prevention of thromboembolism
- Prevention of peri-operative and peri-partum thromboembolism

2 DOSAGE AND ADMINISTRATION

2.1 Recommended Dose

For intravenous use after reconstitution only

- Each vial of THROMBATE III has the functional activity, in International Units (units), stated on the label of the vial. The potency assignment has been determined with a standard calibrated against a World Health Organization antithrombin (AT) reference preparation. When prepared as directed, the approximate final concentration is 50 units per milliliter.
- A guide for dosing THROMBATE III is provided in Table 1.

Table 1: Recommended Dosing Guidelines
Regimen (timing) | Target AT Level | Dose (Units) | Monitor AT Level
Loading Dose [The dose calculation is based on an expected incremental in vivo recovery of 1.4% per unit per kilogram above baseline or trough levels.] | 120% of normal [Expressed as % normal level based on functional AT assay.] | 120 % - baseline % x body weight (kg) 1.4% | - baseline - 20 minutes (peak) post-injection - 12 hours post-injection - pre-injection (trough)
Dose Adjustment (adjust as needed) | 80% to 120% of normal | Target % - trough % x body weight (kg) 1.4% | - 20 minutes (peak) post-injection - at least every 12 hours post-injection - pre-injection (trough)
Maintenance Dose (approximately every 24 hours, adjust as needed) | 80% to 120% of normal | Loading Dose x 0.6 | - approximately every 24 hours, as needed

- Monitor functional plasma levels of AT [see Table 1 and Warnings and Precautions (5.3)] and adjust subsequent dosing based on the trough level achieved with the preceding dose until predictable peak and trough levels have been achieved, generally between 80% to 120% of normal.
- Maintain plasma AT levels between 80% to 120% by administering maintenance doses of 60% of the loading dose, administered every 24 hours. Adjust the maintenance dose and interval between doses based on actual plasma AT levels achieved.
- Individualize the exact loading and maintenance dose and/or dose intervals for each patient based on the individual clinical conditions, response to therapy, and actual plasma AT levels achieved. Recovery of THROMBATE III may vary by patient. For example,
  - The half-life of AT has been reported to be shortened following surgery, hemorrhage or acute thrombosis, and during intravenous heparin (or low molecular weight heparin) administration. In such conditions, monitor plasma AT levels more frequently, and administer THROMBATE III as necessary. [see Warnings and Precautions (5.3), Drug Interactions (7)]
  - When an infusion of THROMBATE III is indicated for a patient with hereditary deficiency to control an acute thrombotic episode or prevent thrombosis during or following surgical or obstetrical procedures, raise the AT level to normal and maintain this level for 2 to 8 days, depending on the indication for treatment, type and extent of surgery, patient’s medical condition, past history and physician’s judgment. Base the concomitant administration of heparin in each of these situations on the medical judgment of the physician. [see Drug Interactions (7)]

2.2 Reconstitution

1. Warm THROMBATE III and Sterile Water for Injection, USP (diluent) vials to room temperature before reconstitution.
2. Remove shrink band from the THROMBATE III vial. If the shrink band is absent or shows signs of tampering, do not use the product and notify Grifols Therapeutics LLC immediately.
3. Remove the plastic flip top from each vial (Fig. A). Cleanse each vial stopper with an alcohol swab and allow surface to dry.
4. Carefully remove the plastic sheath from the short end of the transfer needle. Insert the exposed needle into the diluent vial to the hub (Fig. B).
5. Carefully grip the sheath of the other end of the transfer needle and twist to remove it.
6. Invert the diluent vial and insert the attached needle into the THROMBATE III vial at a 45° angle (Fig. C). This will direct the stream of diluent against the wall of the vial and minimize foaming. The vacuum will draw the diluent into the THROMBATE III vial.*
7. When diluent transfer is complete, remove the diluent vial and transfer needle (Fig. D).
8. Immediately after adding the diluent, swirl the THROMBATE III vial continuously until the product is completely dissolved (Fig. E). Some foaming may occur, but attempt to avoid excessive foaming. Visually inspect the vial for particulate matter and discoloration prior to administration.
9. Clean the top of the vial of reconstituted THROMBATE III again with a new alcohol swab and let surface dry.
10. Attach the filter needle (from the package) to the sterile syringe. Withdraw the THROMBATE III solution into the syringe through the filter needle (Fig. F).
11. Remove the filter needle from the syringe and replace with an appropriate injection or butterfly needle for administration.
12. If the same patient is using more than one vial of THROMBATE III, draw the contents of multiple vials into the same syringe through the filter needles provided.

- If vacuum is lost in the THROMBATE III vial during reconstitution, use a sterile syringe to remove the sterile water from the diluent vial and inject it into the THROMBATE III vial, directing the stream of fluid against the wall of the vial.

2.3 Administration

- Visually inspect parenteral drug products for particulate matter and discoloration prior to administration, whenever solution and container permit.
- Administer THROMBATE III, once reconstituted, alone without mixing with other agents or diluents.
- Administer within 3 hours following reconstitution. Do not refrigerate after reconstitution.
- Adapt the rate of administration to the response of the individual patient, but administration of the entire dose in 10 to 20 minutes is generally well tolerated.

3 DOSAGE FORMS AND STRENGTHS

THROMBATE III is a sterile lyophilized powder for reconstitution in single-dose vials. Each vial of THROMBATE III contains the labeled amount of antithrombin in units per vial, typically 500 units. When reconstituted with 10 mL of Sterile Water for Injection, USP, the final concentration is approximately 50 units per mL.

The potency is determined with a standard calibrated in International Units against a World Health Organization (WHO) antithrombin reference preparation.

4 CONTRAINDICATIONS

None.

5 WARNINGS AND PRECAUTIONS

5.1 Hypersensitivity Reactions

Hypersensitivity reactions, including anaphylaxis, may occur with THROMBATE III infusion. Early signs of hypersensitivity reactions, which can progress to anaphylaxis, may include angioedema, chest tightness, hypotension, rash, nausea, vomiting, paresthesia, restlessness, wheezing and dyspnea. If hypersensitivity symptoms occur, discontinue use of the product immediately and administer appropriate emergency treatment.

5.2 Transmission of Infectious Agents

Because THROMBATE III is made from human blood, it may carry a risk of transmitting infectious agents, e.g., viruses, the variant Creutzfeldt-Jakob disease (vCJD) agent and, theoretically, the Creutzfeldt-Jakob disease (CJD) agent. There is also the possibility that unknown infectious agents may be present in the product. The risk that the product will transmit viruses has been reduced by screening plasma donors for prior exposure to certain viruses, by testing for the presence of certain current virus infections, and by inactivating and removing certain viruses during manufacture. Despite these measures, this product may still potentially transmit diseases.

Report all infections suspected by a physician possibly to have been transmitted by this product to Grifols Therapeutics LLC at 1-800-520-2807.

5.3 Monitoring: Laboratory Tests

- The effect of drugs that use antithrombin to exert their anticoagulation may be altered when THROMBATE III is added or withdrawn. Regularly perform coagulation tests suitable for the anticoagulant used (e.g., aPTT and anti-Factor Xa activity) to avoid excessive or insufficient anticoagulation. Additionally, monitor the patients for the occurrence of bleeding or thrombosis. [see Drug Interactions (7)]
- Measure functional levels of AT in plasma by amidolytic assays using chromogenic substrates or by clotting assays. Do not use immunoassays because they do not detect all hereditary AT deficiencies.

6 ADVERSE REACTIONS

6.1 Clinical Trials Experience

Because clinical studies are conducted under widely varying conditions, adverse reaction rates observed in the clinical trials of one drug cannot be directly compared to rates in other clinical trials of another drug and may not reflect the rates observed in clinical practice.

Two clinical trials were conducted in 33 patients with congenital AT deficiency. The first was a prospective, open-label, dose-escalation, dose-ranging, and pharmacokinetic study in 11 asymptomatic patients. Eight patients received a single dose, escalated sequentially, followed by weekly dose ranging from 25 to 125 unit/kg. Five patients (including 2 from the first part of the study) received weekly THROMBATE III for periods of up to 23 weeks in doses ranging from 125 to 225 unit/kg. The second trial was a phase III, prospective, open-label study conducted in 24 patients for additional kinetics (n=3), the prevention of thrombosis (n=13) during high risk conditions (pregnancy, surgery), or the treatment of thrombosis (n=10). Loading doses targeted an AT plasma level of 120% and ranged from 33 to 150 unit/kg. Maintenance doses targeted a plasma AT range of 70% to 120%, which were 23 to 75 unit/kg.

Adverse reactions reported during the 2 clinical trials are listed in Table 2. Nine patients (27%) experienced 29 adverse reactions which occurred during 17 of 389 infusions. There were no serious adverse reactions reported. The severity of adverse reactions was reported as mild or moderate, except for wound secretion and hematoma, which was severe.

Table 2: Adverse Reactions Occurring during Hereditary Deficiency Trials
Adverse Reaction | By Patients N (%) (N=33 Patients) | By Infusions N (%) (N=389 Infusions)
Any adverse reaction | 9 (27) | 29 (7.5)
Dizziness | 4 (12) | 8 (2.1)
Chest discomfort | 3 (9) | 3 (0.8)
Nausea | 3 (9) | 3 (0.8)
Dysgeusia | 2 (6) | 3 (0.8)
Pain (cramps) | 2 (6) | 2 (0.5)
Chills | 1 (3) | 2 (0.5)
Wound secretion and hematoma | 1 (3) | 2 (0.5)
Vision blurred | 1 (3) | 1 (0.3)
Chest pain | 1 (3) | 1 (0.3)
Dyspnea | 1 (3) | 1 (0.3)
Intestinal dilatation | 1 (3) | 1 (0.3)
Pyrexia | 1 (3) | 1 (0.3)
Urticaria | 1 (3) | 1 (0.3)

During clinical investigation of THROMBATE III, there were no reports of virus transmission. None of 12 patients monitored for a median of 8 months (range 2–19 months) after receiving THROMBATE III became antibody positive to human immunodeficiency virus (HIV-1). None of 14 patients monitored for ≥ 3 months demonstrated any evidence of hepatitis.

7 DRUG INTERACTIONS

The anticoagulant effect of heparin is enhanced by concurrent treatment with THROMBATE III in patients with hereditary AT deficiency. Thus, in order to avoid bleeding, the dosage of heparin (or low molecular weight heparin) may need to be reduced during treatment with THROMBATE III.

The effect of drugs that use antithrombin to exert their anticoagulation may be altered when THROMBATE III is added or withdrawn. Regularly perform coagulation tests suitable for the anticoagulant used (e.g., aPTT and anti-Factor Xa activity) and at close intervals to avoid excessive or insufficient anticoagulation. Adjust dosage of anticoagulant as necessary. Additionally, monitor the patients for the occurrence of bleeding or thrombosis.

8 USE IN SPECIFIC POPULATIONS

8.1 Pregnancy

Risk Summary

There are no data with THROMBATE III use in pregnant women to inform a drug-associated risk. However, there are clinical considerations [see Clinical Considerations]. It is not known whether THROMBATE III can cause fetal harm when administered to a pregnant woman or can affect reproduction capacity. THROMBATE III should be given to a pregnant woman only if clearly needed. In the U.S. general population, the estimated background risk of major birth defects and miscarriage in clinically recognized pregnancies is 2-4% and 15-20%, respectively.

Reproduction studies have been performed in rats and rabbits at doses up to four times the human dose and have revealed no evidence of impaired fertility or harm to the fetus due to THROMBATE III.

Clinical Considerations

Labor or Delivery

Suspend heparin (or low molecular weight heparin) administration and continue THROMBATE III administration during labor and delivery.

8.2 Lactation

Risk Summary

There is no information regarding the presence of THROMBATE III in human milk, the effects on the breastfed infant, or the effects on milk production. The developmental and health benefits of breastfeeding should be considered along with the mother’s clinical need for THROMBATE III and any potential adverse effects on the breastfed infant from THROMBATE III or from the underlying maternal condition.

8.4 Pediatric Use

The safety and effectiveness of THROMBATE III have been established in pediatric patients. The use of THROMBATE III in pediatric patients with hereditary antithrombin (AT) deficiency was supported by extrapolation of data from two clinical trials in adult patients [see Adverse Reactions (6) and Clinical Studies (14)].

8.5 Geriatric Use

The safety and effectiveness in the geriatric population have not been established.

11 DESCRIPTION

THROMBATE III, antithrombin III (human), is a sterile, non-pyrogenic concentrate of human antithrombin (AT) in lyophilized powder form for reconstitution for intravenous injection. When reconstituted with Sterile Water for Injection, USP, THROMBATE III has a pH of 6.0 to 7.5 and contains 110 mEq/L to 210 mEq/L sodium, 110 mEq/L to 210 mEq/L chloride, 0.075 M to 0.125 M alanine, and not more than 0.1 unit of heparin per 1 unit of AT. THROMBATE III contains no preservative.

THROMBATE III is prepared from pooled units of human plasma from normal donors. The capacity of the THROMBATE III manufacturing process to remove and/or inactivate enveloped and non-enveloped viruses has been validated by laboratory spiking studies on a scaled down process model using a wide range of viruses with diverse physicochemical properties. There are two dedicated virus inactivation/removal steps included in the THROMBATE III manufacturing process: a heat treatment step at 60°C ± 0.5°C for not less than 10 hours for virus inactivation and a nanofiltration step for effective removal of viruses as small as 18 nm.

The THROMBATE III manufacturing process was also investigated for its capacity to decrease the infectivity of an experimental agent of transmissible spongiform encephalopathy (TSE), considered as a model for the variant Creutzfeldt-Jakob disease (vCJD) and Creutzfeldt-Jakob disease (CJD) agents. An individual production step in the THROMBATE III manufacturing process has been shown to decrease TSE infectivity of that experimental model agent. The TSE reduction step is the Effluent I to Effluent II + III fractionation step (6.0 log10). These studies provide reasonable assurance that low levels of vCJD/CJD agent infectivity, if present in the starting material, would be removed.

12 CLINICAL PHARMACOLOGY

12.1 Mechanism of Action

Antithrombin, an alpha2-glycoprotein of molecular weight 58,000, is normally present in human plasma at a concentration of approximately 12.5 mg/dL and is the major plasma inhibitor of thrombin. Inactivation of thrombin by AT occurs by formation of a covalent bond resulting in an inactive 1:1 stoichiometric complex between the two, involving an interaction of the active serine of thrombin and an arginine reactive site on AT. AT is also capable of inactivating other components of the coagulation cascade including factors IXa, Xa, XIa, and XIIa, as well as plasmin. The neutralization rate of serine proteases by AT proceeds slowly in the absence of heparin but is greatly accelerated in the presence of heparin. As the therapeutic antithrombotic effect of heparin is mediated by AT, heparin in vivo is ineffective in the absence or near absence of AT.

After administration, THROMBATE III temporarily replaces the missing AT in patients with hereditary antithrombin deficiency.

12.3 Pharmacokinetics

In a clinical trial of THROMBATE III conducted in asymptomatic patients with hereditary deficiency of AT, 8 patients were administered a single dose of THROMBATE III at doses ranging from 25 units/kg to 125 units/kg. Pharmacokinetic parameters were determined using immunologic and functional AT assays (Table 3).

Table 3: Pharmacokinetic Analyses of THROMBATE III in Asymptomatic Patients with Congenital AT Deficiency
 | Immunological Assay | Functional Assay
AT recovery, % / unit / kg | 1.6 ± 0.1 [Mean ± SEM] | 1.4 ± 0.1
50% disappearance time, hr | 17.4 ± 3.9 | 22.3 ± 8.6
t½, day | 2.5 ± 1.5 | 3.8 ± 1.8

14 CLINICAL STUDIES

In a prospective, open-label clinical trial, 21 patients were administered THROMBATE III for 16 prophylaxis events (n=13 patients) and 10 for treatment of thrombosis (n=10 patients) with 2 patients receiving THROMBATE III for both prophylaxis and treatment of thrombosis. None of the 13 patients with hereditary AT deficiency and histories of thromboembolism treated prophylactically on 16 separate occasions with THROMBATE III for high thrombotic risk situations (11 surgical procedures, 5 pregnancies and/or deliveries) developed a thrombotic complication. Heparin was administered in 3 of the 11 surgical procedures. Two of the pregnant patients received LMW heparin prophylactically during the first trimester, but which was unable to maintain anti-coagulation with increasing dosages. [see Drug Interactions (7)] They experienced a thrombosis, which subsequently resolved with the addition of THROMBATE III, and were therefore administered THROMBATE III and LMW heparin prophylaxis weekly during the second and third trimesters, and during labor and delivery. These two patients did not experience a new thrombosis.

Ten patients with hereditary AT deficiency were treated with THROMBATE III as well as heparin (n=9) for major thrombotic or thromboembolic complications, including 4 patients with thrombosis during the first trimester of pregnancy. Nine patients recovered with no additional thromboses or extension of existing thrombosis. The tenth patient died due to complications from the original pulmonary embolism with infarction which preceded treatment with THROMBATE III.

16 HOW SUPPLIED/STORAGE AND HANDLING

THROMBATE III is supplied in a kit containing one single-dose vial of THROMBATE III lyophilized powder for reconstitution, one vial of Sterile Water for Injection, USP, one sterile double-ended transfer needle, and one sterile filter needle. The total activity of AT in International Units is stated on the label of the THROMBATE III vial.

Components of the packaging do not contain natural rubber latex.

NDC Number Carton (Kit) | Approximate Antithrombin Potency | Diluent
13533-603-20, 13533-602-50 or 13533-606-12 | 500 units | 10 mL

- Store THROMBATE III at temperatures not to exceed 25°C (77°F).
- Avoid freezing as breakage of the diluent vial might occur.

17 PATIENT COUNSELING INFORMATION

Discuss the following with the patient and/or caregiver.

- Hypersensitivity Reactions: Inform patient and/or caregiver that allergic-type hypersensitivity reactions are possible and instruct them to inform their physicians about any past or present known hypersensitivity to human plasma proteins prior to treatment with THROMBATE III. Inform patients of the early signs of hypersensitivity reactions including hives, generalized urticaria, tightness of the chest, wheezing, hypotension, and anaphylaxis and to notify their health care provider immediately if these events develop. [see Warnings and Precautions (5.1)]
- Transmission of Infectious Disease: Inform patient and/or caregiver that THROMBATE III is made from human plasma and may carry a risk of transmitting infectious agents that can cause disease (e.g., viruses, the variant Creutzfeldt-Jakob disease (vCJD) agent and, theoretically, the Creutzfeldt-Jakob disease (CJD) agent). Inform patients that this risk has been reduced by screening plasma donors for prior exposure to certain infectious agents, by testing the donated plasma for markers of certain current infections, and by inactivating and/or removing pathogens during manufacturing. [see Warnings and Precautions (5.2)]

Manufactured by:
GRIFOLS
Grifols Therapeutics LLC
Research Triangle Park, NC 27709 USA
U.S. License No. 1871
3070188

PACKAGE LABEL

NDC 13533-605-21
10 mL
Antithrombin III
(Human)
Thrombate III®
Lyophilized Powder
Rx only
For Intravenous
Administration Only
Heat-Treated Nanofiltered
The patient and physician should discuss
the risks and benefits of this product.
No Preservative
Sterile — Nonpyrogenic
Reconstitute with 10 mL Sterile Water for
Injection, USP.
Store at temperatures not to exceed 25°C
(77°F). Do not freeze.
Dosage and Administration: Read package
insert.
Grifols Therapeutics LLC
Research Triangle Park, NC 27709 USA
U.S. License No. 1871
3065424
Lot
Exp.
IU

NDC 13533-602-50 10 mL
Antithrombin III (Human)
Thrombate III®
Lyophilized Powder
Rx only
For Intravenous Administration Only
GRIFOLS
Heat-Treated
Nanofiltered
Contents:
One vial of THROMBATE III
10 mL Sterile Water for Injection,
USP
One sterile filter needle
One sterile double-ended transfer
needle
No Preservative
Sterile — Nonpyrogenic
GRIFOLS
The patient and physician should discuss the risks and benefits of
this product.
This product when reconstituted with 10 mL Sterile Water for
Injection, USP, contains 110-210 mEq/L sodium, 110-210 mEq/L
chloride, 0.075-0.125 M alanine, and not more than
0.1 IU heparin/IU ATIII.
Administer within 3 hours after reconstitution.
Dosage and Administration: Read enclosed package insert.
Store at temperatures not to exceed 25°C (77°F). Do not
freeze.
If the shrink band is absent or shows any sign of tampering, do not
use the product and notify Grifols Therapeutics LLC immediately.
Not Returnable for Credit or Exchange
GRIFOLS
This product is prepared from large
pools of human plasma which may
contain infectious agents.
See package insert Warnings.
Grifols Therapeutics LLC
Research Triangle Park,
NC 27709 USA
U.S. License No. 1871
GRIFOLS
Open other end
Carton: 3065431
GTIN XXXXXXXXXXXXXX
LOT XXXXXXXXXX
EXP DDMMMYYYY
SN 4001XXXXXXXXXX
IU XXX
NDC 13533-602-50 10 mL
Antithrombin III (Human)
Thrombate III®

NDC 13533-200-10
Sterile Water for Injection, USP
10 mL
Rx Only
For reconstitution of accompanying product
Single-Dose Container, Nonpyrogenic
Do not use unless clear. No antimicrobial agent or other
substance has been added. Do not use for intravascular
injection without making approximately isotonic by
addition of suitable solute. Discard unused portion.
Mfd by: Laboratorios Grifols, S. A., Parets del Vallès, Barcelona, 08150 Spain
Mfd for: Grifols Therapeutics LLC, Research Triangle Park, NC, 27709 USA
3051810
Lot / Exp.

NDC 76297-002-12
Sterile Water for Injection, USP
10 mL
Rx Only
For reconstitution of accompanying product
Single-Dose Container, Nonpyrogenic
Do not use unless clear. No antimicrobial agent or other
substance has been added. Do not use for intravascular
injection without making approximately isotonic by
addition of suitable solute. Discard unused portion.
Mfd by: Laboratorios Grifols, S. A. Parets del Vallès,
Barcelona 08150 Spain
3057423
Lot
EXP